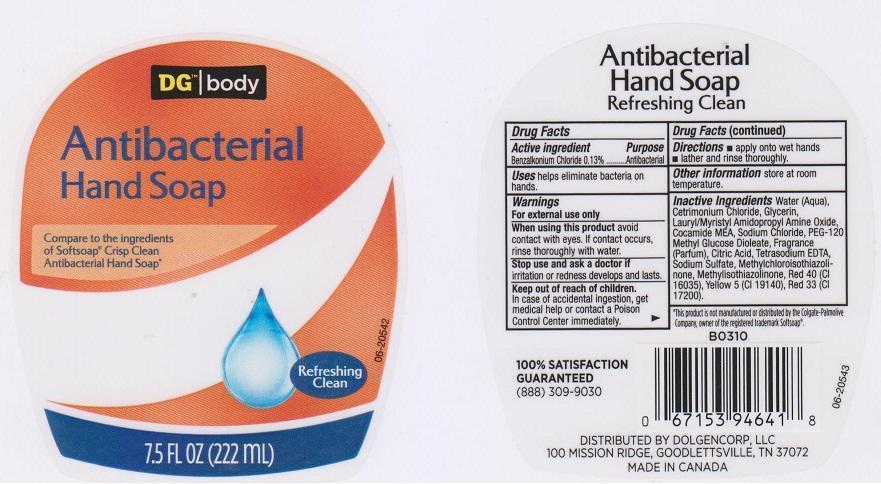 DRUG LABEL: DG BODY
NDC: 55910-721 | Form: LIQUID
Manufacturer: DOLGENCORP INC
Category: otc | Type: HUMAN OTC DRUG LABEL
Date: 20150702

ACTIVE INGREDIENTS: BENZALKONIUM CHLORIDE 1.3 mg/1 mL
INACTIVE INGREDIENTS: WATER; CETRIMONIUM CHLORIDE; GLYCERIN; LAURAMIDOPROPYLAMINE OXIDE; COCO MONOETHANOLAMIDE; SODIUM CHLORIDE; PEG-120 METHYL GLUCOSE DIOLEATE; CITRIC ACID MONOHYDRATE; EDETATE SODIUM; SODIUM SULFATE; METHYLCHLOROISOTHIAZOLINONE; METHYLISOTHIAZOLINONE; FD&C RED NO. 40; FD&C YELLOW NO. 5; D&C RED NO. 33

DRUG FACTS

ACTIVE INGREDIENT

BENZALKONIUM CHLORIDE 0.13%

PURPOSE

ANTIBACTERIAL

USES

HELPS ELIMINATE BACTERIA ON HANDS

WARNINGS

FOR EXTERNAL USE ONLY

WHEN USING THIS PRODUCT

AVOID CONTACT WITH EYES. IF CONTACT OCCURS, RINSE THOROUGHLY WITH WATER

STOP USE AND ASK A DOCTOR

IF IRRITATION OR REDNESS DEVELOPS AND LASTS

KEEP OUT OF REACH OF CHILDREN

IN CASE OF ACCIDENTAL INGESTION, GET MEDICAL HELP OR CONTACT A POISON CONTROL CENTER IMMEDIATELY

DIRECTIONS

- APPLY ONTO WET HANDS
- LATHER AND RINSE THOROUGHLY

OTHER INFORMATION

STORE AT ROOM TEMPERATURE

INACTIVE INGREDIENTS

WATER (AQUA), CETRIMONIUM CHLORIDE, GLYCERIN, LAURYL/MYRISTYL AMIDOPROPYL AMINE OXIDE, COCAMIDE MEA, SODIUM CHLORIDE, PEG-120 METHYL GLUCOSE DIOLEATE, FRAGRANCE (PARFUM), CITRIC ACID, TETRASODIUM EDTA, SODIUM SULFATE, METHYLCHLOROISOTHIAZOLINONE, METHYLISOTHIAZOLINONE, RED 40 (CI 16035), YELLOW 5 (CI 19140), RED 33 (CI 17200)